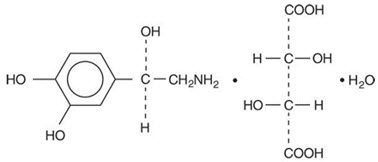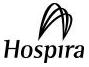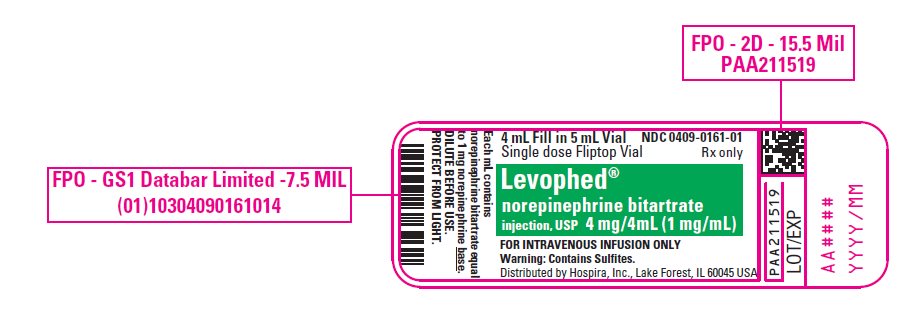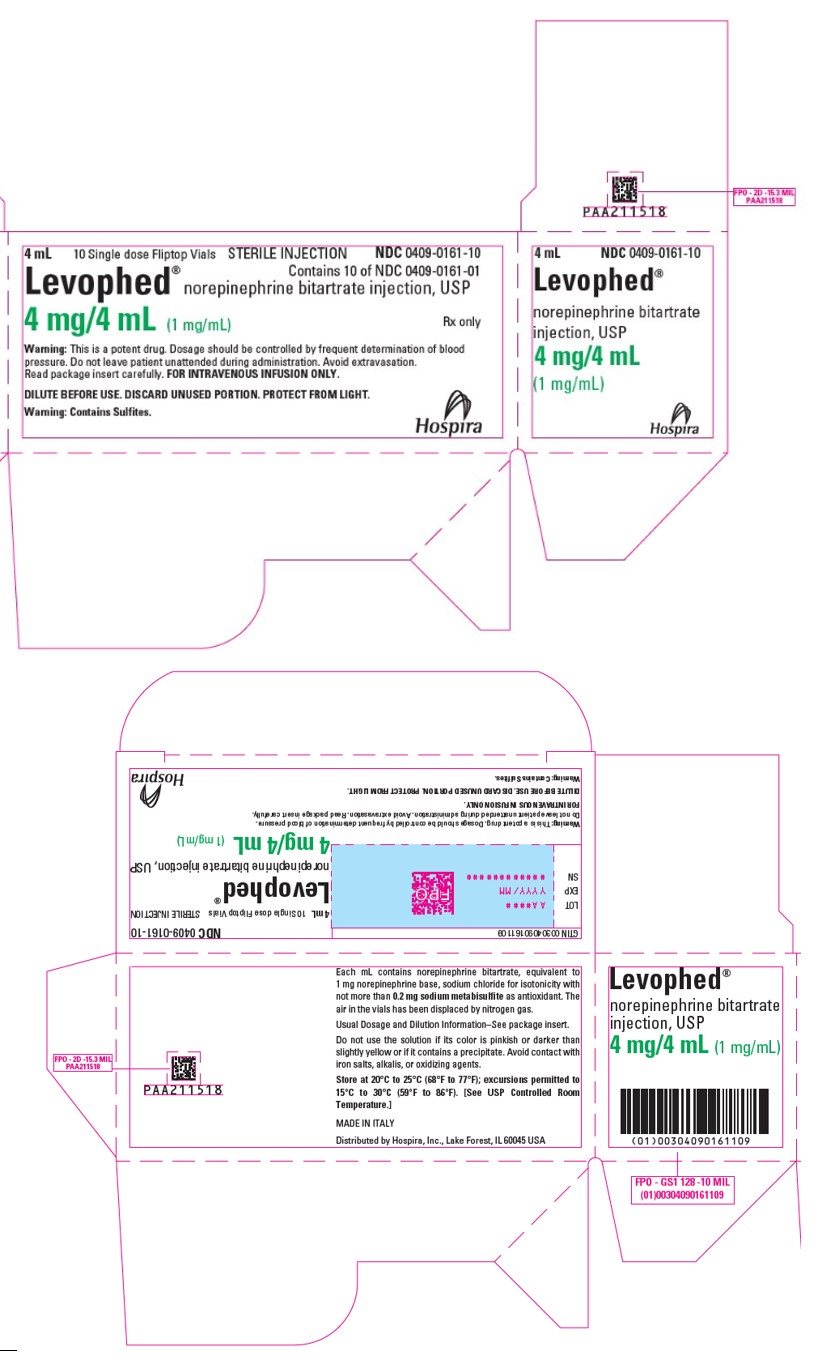 DRUG LABEL: LEVOPHED
NDC: 0409-0161 | Form: INJECTION, SOLUTION, CONCENTRATE
Manufacturer: Hospira, Inc.
Category: prescription | Type: HUMAN PRESCRIPTION DRUG LABEL
Date: 20250612

ACTIVE INGREDIENTS: NOREPINEPHRINE BITARTRATE 1 mg/1 mL
INACTIVE INGREDIENTS: SODIUM CHLORIDE; SODIUM METABISULFITE

HIGHLIGHTS OF PRESCRIBING INFORMATION

These highlights do not include all the information needed to use LEVOPHED safely and effectively. See full prescribing information for LEVOPHED.
LEVOPHED® (norepinephrine bitartrate) injection, for intravenous use
Initial U.S. Approval: 1950

1 INDICATIONS AND USAGE

LEVOPHED is a catecholamine indicated for restoration of blood pressure in adult patients with acute hypotensive states. (1)

2 DOSAGE AND ADMINISTRATION

- Initial dose of 0.25 mL to 0.375 mL (from 8 mcg to 12 mcg of base) per minute, adjust the rate of flow to establish and maintain a low to normal blood pressure (usually 80 mm Hg to 100 mm Hg systolic) sufficient to maintain the circulation of vital organs. (2.2)
- The average maintenance dose ranges from 0.0625 mL to 0.125 mL per minute (from 2 mcg to 4 mcg of base). (2.2)

3 DOSAGE FORMS AND STRENGTHS

Injection: 4 mg/4 mL (1 mg/mL) norepinephrine base in single-dose glass vial. (3)

4 CONTRAINDICATIONS

None. (4)

5 WARNINGS AND PRECAUTIONS

- Tissue Ischemia: Avoid extravasation of LEVOPHED into the tissues, as local necrosis might ensue due to the vasoconstrictive action of the drug. Infuse LEVOPHED into a large vein. To prevent sloughing and necrosis in areas in which extravasation has taken place, the area should be infiltrated as soon as possible with 10 mL to 15 mL of saline solution containing from 5 mg to 10 mg of an adrenergic blocking agent. (5.1)
- Hypotension After Abrupt Discontinuation: Sudden cessation of the infusion rate may result in marked hypotension. Reduce the LEVOPHED infusion rate gradually. (5.2)
- Cardiac Arrhythmias: LEVOPHED may cause arrhythmias. Monitor cardiac function in patients with underlying heart disease. (5.3)
- Allergic Reactions with Sulfite: LEVOPHED contains sodium metabisulfite. Sulfite may cause allergic-type-reactions. (5.4)

6 ADVERSE REACTIONS

Most common adverse reactions are ischemic injury, bradycardia, anxiety, transient headache, respiratory difficulty, and extravasation necrosis at injection site. (6)
To report SUSPECTED ADVERSE REACTIONS, contact Pfizer Inc. at 1-800-438-1985, or FDA at 1-800-FDA-1088 or www.fda.gov/medwatch.

7 DRUG INTERACTIONS

- Monoamine oxidase inhibitors (MAOI) or antidepressants of the triptyline or imipramine types may result in hypertension. (7.1)
- Cyclopropane and halothane anesthetics increase cardiac autonomic irritability. (7.4)

8 USE IN SPECIFIC POPULATIONS

- Elderly patients may be at greater risk of developing adverse reactions. (8.5)

FULL PRESCRIBING INFORMATION

1 INDICATIONS AND USAGE

LEVOPHED is indicated to raise blood pressure in adult patients with severe, acute hypotension.

2 DOSAGE AND ADMINISTRATION

2.1 Important Dosage and Administration Instructions

Correct Hypovolemia

Address hypovolemia before initiation of LEVOPHED therapy. If the patient does not respond to therapy, suspect occult hypovolemia [see Warnings and Precautions (5.1)].

Administration

Dilute LEVOPHED prior to use [see Dosage and Administration (2.3)].

Infuse LEVOPHED into a large vein. Avoid infusions into the veins of the leg in the elderly or in patients with occlusive vascular disease of the legs [see Warnings and Precautions (5.1)]. Avoid using a catheter-tie-in technique.

Discontinuation

When discontinuing the infusion, reduce the flow rate gradually. Avoid abrupt withdrawal.

2.2 Dosage

After an initial dosage of 8 to 12 mcg per minute via intravenous infusion, assess patient response and adjust dosage to maintain desired hemodynamic effect. Monitor blood pressure every two minutes until the desired hemodynamic effect is achieved, and then monitor blood pressure every five minutes for the duration of the infusion.

Typical maintenance intravenous dosage is 2 to 4 mcg per minute.

2.3 Preparation of Diluted Solution

Visually inspect LEVOPHED for particulate matter and discoloration prior to administration (the solution is colorless). Do not use the solution if its color is pinkish or darker than slightly yellow or if it contains a precipitate.

Add the content of one LEVOPHED vial (4 mg in 4 mL) to 1,000 mL of 5% Dextrose Injection, USP or Sodium Chloride Injection solutions that contain 5% dextrose to produce a 4 mcg per mL dilution. Dextrose reduces loss of potency due to oxidation. Administration in saline solution alone is not recommended.

Use higher concentration solutions in patients requiring fluid restriction. Prior to use, store the diluted LEVOPHED solution for up to 24 hours at room temperature [20°C to 25°C (68°F to 77°F)] and protect from light.

2.4 Drug Incompatibilities

Avoid contact with iron salts, alkalis, or oxidizing agents.

Whole blood or plasma, if indicated to increase blood volume, should be administered separately.

3 DOSAGE FORMS AND STRENGTHS

Injection: 4 mg/4 mL (1 mg/mL norepinephrine base) sterile, colorless solution in a single-dose amber glass vial.

4 CONTRAINDICATIONS

None.

5 WARNINGS AND PRECAUTIONS

5.1 Tissue Ischemia

Administration of LEVOPHED to patients who are hypotensive from hypovolemia can result in severe peripheral and visceral vasoconstriction, decreased renal perfusion and reduced urine output, tissue hypoxia, lactic acidosis, and reduced systemic blood flow despite "normal" blood pressure. Address hypovolemia prior to initiating LEVOPHED [see Dosage and Administration (2.1)]. Avoid LEVOPHED in patients with mesenteric or peripheral vascular thrombosis, as this may increase ischemia and extend the area of infarction.

Gangrene of the extremities has occurred in patients with occlusive or thrombotic vascular disease or who received prolonged or high dose infusions. Monitor for changes to the skin of the extremities in susceptible patients.

Extravasation of LEVOPHED may cause necrosis and sloughing of surrounding tissue. To reduce the risk of extravasation, infuse into a large vein, check the infusion site frequently for free flow, and monitor for signs of extravasation [see Dosage and Administration (2.1)].

Emergency Treatment of Extravasation

To prevent sloughing and necrosis in areas in which extravasation has occurred, infiltrate the ischemic area as soon as possible, using a syringe with a fine hypodermic needle with 5 to 10 mg of phentolamine mesylate in 10 to 15 mL of 0.9% Sodium Chloride Injection in adults.

Sympathetic blockade with phentolamine causes immediate and conspicuous local hyperemic changes if the area is infiltrated within 12 hours.

5.2 Hypotension after Abrupt Discontinuation

Sudden cessation of the infusion rate may result in marked hypotension. When discontinuing the infusion, gradually reduce the LEVOPHED infusion rate while expanding blood volume with intravenous fluids.

5.3 Cardiac Arrhythmias

LEVOPHED elevates intracellular calcium concentrations and may cause arrhythmias, particularly in the setting of hypoxia or hypercarbia. Perform continuous cardiac monitoring of patients with arrhythmias.

5.4 Allergic Reactions Associated with Sulfite

LEVOPHED contains sodium metabisulfite, a sulfite that may cause allergic-type reactions including anaphylactic symptoms and life-threatening or less severe asthmatic episodes in certain susceptible people. The overall prevalence of sulfite sensitivity in the general population is unknown. Sulfite sensitivity is seen more frequently in asthmatic than in non-asthmatic people.

6 ADVERSE REACTIONS

The following adverse reactions are described in greater detail in other sections:

- Tissue Ischemia [see Warnings and Precautions (5.1)]
- Hypotension [see Warnings and Precautions (5.2)]
- Cardiac Arrhythmias [see Warnings and Precautions (5.3)]

The most common adverse reactions are hypertension and bradycardia.

The following adverse reactions can occur:

Nervous system disorders: Anxiety, headache

Respiratory disorders: Respiratory difficulty, pulmonary edema

7 DRUG INTERACTIONS

7.1 MAO-Inhibiting Drugs

Co-administration of LEVOPHED with monoamine oxidase (MAO) inhibitors or other drugs with MAO-inhibiting properties (e.g., linezolid) can cause severe, prolonged hypertension.

If administration of LEVOPHED cannot be avoided in patients who recently have received any of these drugs and in whom, after discontinuation, MAO activity has not yet sufficiently recovered, monitor for hypertension.

7.2 Tricyclic Antidepressants

Co-administration of LEVOPHED with tricyclic antidepressants (including amitriptyline, nortriptyline, protriptyline, clomipramine, desipramine, imipramine) can cause severe, prolonged hypertension. If administration of LEVOPHED cannot be avoided in these patients, monitor for hypertension.

7.3 Antidiabetics

LEVOPHED can decrease insulin sensitivity and raise blood glucose. Monitor glucose and consider dosage adjustment of antidiabetic drugs.

7.4 Halogenated Anesthetics

Concomitant use of LEVOPHED with halogenated anesthetics (e.g., cyclopropane, desflurane, enflurane, isoflurane, and sevoflurane) may lead to ventricular tachycardia or ventricular fibrillation. Monitor cardiac rhythm in patients receiving concomitant halogenated anesthetics.

8 USE IN SPECIFIC POPULATIONS

8.1 Pregnancy

Risk Summary

Limited published data consisting of a small number of case reports and multiple small trials involving the use of norepinephrine in pregnant women at the time of delivery have not identified an increased risk of major birth defects, miscarriage or adverse maternal or fetal outcomes. There are risks to the mother and fetus from hypotension associated with septic shock, myocardial infarction and stroke which are medical emergencies in pregnancy and can be fatal if left untreated. (see Clinical Considerations). In animal reproduction studies, using high doses of intravenous norepinephrine resulted in lowered maternal placental blood flow. Clinical relevance to changes in the human fetus is unknown since the average maintenance dose is ten times lower (see Data). Increased fetal reabsorptions were observed in pregnant hamsters after receiving daily injections at approximately 2 times the maximum recommended dose on a mg/m^3 basis for four days during organogenesis (see Data).

The estimated background risk for major birth defects and miscarriage for the indicated population is unknown. All pregnancies have a background risk of birth defect, loss, or other adverse outcomes. In the U.S. general population, the estimated background risk of major birth defects and miscarriage in the clinically recognized pregnancies is 2–4% and 15–20%, respectively.

Clinical Considerations

Disease-associated maternal and/or embryo/fetal risk

Hypotension associated with septic shock, myocardial infarction, and stroke are medical emergencies in pregnancy which can be fatal if left untreated. Delaying treatment in pregnant women with hypotension associated with septic shock, myocardial infarction and stroke may increase the risk of maternal and fetal morbidity and mortality. Life-sustaining therapy for the pregnant woman should not be withheld due to potential concerns regarding the effects of norepinephrine on the fetus.

Data

Animal Data

A study in pregnant sheep receiving high doses of intravenous norepinephrine (40 mcg/min, at approximately 10 times the average maintenance dose of 2–4 mcg/min in human, on a mg/kg basis) exhibited a significant decrease in maternal placental blood flow. Decreases in fetal oxygenation, urine and lung liquid flow were also observed.

Norepinephrine administration to pregnant rats on Gestation Day 16 or 17 resulted in cataract production in rat fetuses.

In hamsters, an increased number of resorptions (29.1% in study group vs. 3.4% in control group), fetal microscopic liver abnormalities and delayed skeletal ossification were observed at approximately 2 times the maximum recommended intramuscular or subcutaneous dose (on a mg/m^2 basis at a maternal subcutaneous dose of 0.5 mg/kg/day from Gestation Day 7–10).

8.2 Lactation

Risk Summary

There are no data on the presence of norepinephrine in either human or animal milk, the effects on the breastfed infant, or the effects on milk production. Clinically relevant exposure to the infant is not expected based on the short half-life and poor oral bioavailability of norepinephrine.

8.4 Pediatric Use

Safety and effectiveness in pediatric patients have not been established.

8.5 Geriatric Use

Clinical studies of LEVOPHED did not include sufficient numbers of subjects aged 65 and over to determine whether they respond differently from younger subjects. Other reported clinical experience has not identified differences in responses between the elderly and younger patients. In general, dose selection for an elderly patient should be cautious, usually starting at the low end of the dosing range, reflecting the greater frequency of decreased hepatic, renal, or cardiac function, and of concomitant disease or other drug therapy.

Avoid administration of LEVOPHED into the veins in the leg in elderly patients [see Warnings and Precautions (5.1)].

10 OVERDOSAGE

Overdosage with LEVOPHED may result in headache, severe hypertension, reflex bradycardia, marked increase in peripheral resistance, and decreased cardiac output.

In case of overdosage, discontinue LEVOPHED until the condition of the patient stabilizes.

11 DESCRIPTION

Norepinephrine (sometimes referred to as l-arterenol/Levarterenol or l-norepinephrine) is a sympathomimetic amine which differs from epinephrine by the absence of a methyl group on the nitrogen atom.

LEVOPHED is (-)-α-(aminomethyl)-3,4-dihydroxybenzyl alcohol tartrate (1:1) (salt) monohydrate (molecular weight 337.3 g/mol) and has the following structural formula:

LEVOPHED is supplied in a sterile aqueous solution in the form of the bitartrate salt to be administered by intravenous infusion. Norepinephrine is sparingly soluble in water, very slightly soluble in alcohol and ether, and readily soluble in acids. Each mL contains 1 mg of norepinephrine base (equivalent to 1.89 mg of norepinephrine bitartrate, anhydrous basis), sodium chloride for isotonicity, not more than 0.2 mg (vials) of sodium metabisulfite as an antioxidant. It has a pH of 3.0 to 4.5. The air in the containers has been displaced by nitrogen gas.

12 CLINICAL PHARMACOLOGY

12.1 Mechanism of Action

Norepinephrine is a peripheral vasoconstrictor (alpha-adrenergic action) and an inotropic stimulator of the heart and dilator of coronary arteries (beta-adrenergic action).

12.2 Pharmacodynamics

The primary pharmacodynamic effects of norepinephrine are cardiac stimulation and vasoconstriction. Cardiac output is generally unaffected, although it can be decreased, and total peripheral resistance is also elevated. The elevation in resistance and pressure result in reflex vagal activity, which slows the heart rate and increases stroke volume. The elevation in vascular tone or resistance reduces blood flow to the major abdominal organs as well as to skeletal muscle. Coronary blood flow is substantially increased secondary to the indirect effects of alpha stimulation. After intravenous administration, a pressor response occurs rapidly and reaches steady state within 5 minutes. The pharmacologic actions of norepinephrine are terminated primarily by uptake and metabolism in sympathetic nerve endings. The pressor action stops within 1–2 minutes after the infusion is discontinued.

12.3 Pharmacokinetics

Absorption

Following initiation of intravenous infusion, the steady state plasma concentration is achieved in 5 min.

Distribution

Plasma protein binding of norepinephrine is approximately 25%. It is mainly bound to plasma albumin and to a smaller extent to prealbumin and alpha 1-acid glycoprotein. The volume of distribution is 8.8 L. Norepinephrine localizes mainly in sympathetic nervous tissue. It crosses the placenta but not the blood-brain barrier.

Elimination

The mean half-life of norepinephrine is approximately 2.4 min. The average metabolic clearance is 3.1 L/min.

Metabolism

Norepinephrine is metabolized in the liver and other tissues by a combination of reactions involving the enzymes catechol-O-methyltransferase (COMT) and MAO. The major metabolites are normetanephrine and 3-methoxyl-4-hydroxy mandelic acid (vanillylmandelic acid, VMA), both of which are inactive. Other inactive metabolites include 3-methoxy-4-hydroxyphenylglycol, 3,4-dihydroxymandelic acid, and 3,4-dihydroxyphenylglycol.

Excretion

Noradrenaline metabolites are excreted in urine primarily as sulphate conjugates and, to a lesser extent, as glucuronide conjugates. Only small quantities of norepinephrine are excreted unchanged.

13 NONCLINICAL TOXICOLOGY

13.1 Carcinogenesis, Mutagenesis, Impairment of Fertility

Carcinogenesis, mutagenesis, and fertility studies have not been performed.

16 HOW SUPPLIED/STORAGE AND HANDLING

LEVOPHED (norepinephrine bitartrate) injection, USP, is a sterile, colorless solution for injection intended for intravenous use. It contains the equivalent of 1 mg of norepinephrine base per 1 mL (4 mg/4 mL). It is available as 4 mg/4 mL in single-dose amber glass vials. Supplied as:

Unit of Sale | Concentration
NDC 0409-0161-10; 10 vials in a Carton | 4 mg/4 mL; (1 mg/mL)

STORAGE AND HANDLING

Store at 20°C to 25°C (68°F to 77°F); excursions permitted to 15°C to 30°C (59°F to 86°F). [See USP Controlled Room Temperature.]

Store in original carton until time of administration to protect from light. Discard unused portion.

17 PATIENT COUNSELING INFORMATION

Risk of Tissue Damage

Advise the patient, family, or caregiver to report signs of extravasation urgently [see Warnings and Precautions (5.1)].

This product's labeling may have been updated. For the most recent prescribing information, please visit www.pfizer.com.

Distributed by Hospira, Inc., Lake Forest, IL 60045 USA

LAB-1579-1.0

PRINCIPAL DISPLAY PANEL - 4 mL Vial Label

4 mL Fill in 5 mL Vial
NDC 0409-0161-01
Single dose Fliptop Vial
Rx only

Levophed®
norepinephrine bitartrate
injection, USP 4 mg/4mL (1 mg/mL)

FOR INTRAVENOUS INFUSION ONLY
Warning: Contains Sulfites.
Distributed by Hospira, Inc., Lake Forest, IL 60045 USA

PRINCIPAL DISPLAY PANEL - 4 mL Vial Carton

4 mL
10 Single dose Fliptop Vials
STERILE INJECTION
NDC 0409-0161-10
Contains 10 of NDC 0409-0161-01

Levophed® norepinephrine bitartrate injection, USP

4 mg/4 mL (1 mg/mL)
Rx only

Warning: This is a potent drug. Dosage should be controlled by frequent determination of blood
pressure. Do not leave patient unattended during administration. Avoid extravasation.
Read package insert carefully. FOR INTRAVENOUS INFUSION ONLY.

DILUTE BEFORE USE. DISCARD UNUSED PORTION. PROTECT FROM LIGHT.

Warning: Contains Sulfites.

Hospira